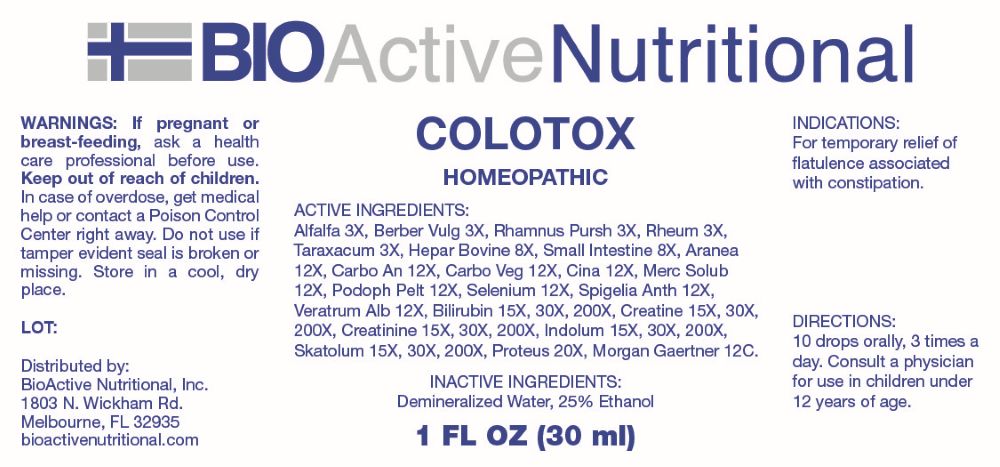 DRUG LABEL: Colotox
NDC: 43857-0801 | Form: LIQUID
Manufacturer: BioActive Nutritional, Inc.
Category: homeopathic | Type: HUMAN OTC DRUG LABEL
Date: 20260120

ACTIVE INGREDIENTS: MEDICAGO SATIVA WHOLE 3 [hp_X]/1 mL; BERBERIS VULGARIS ROOT BARK 3 [hp_X]/1 mL; FRANGULA PURSHIANA BARK 3 [hp_X]/1 mL; RHEUM PALMATUM ROOT 3 [hp_X]/1 mL; TARAXACUM OFFICINALE 3 [hp_X]/1 mL; HEPARIN, BOVINE 8 [hp_X]/1 mL; SUS SCROFA INTESTINAL MUCOSA 8 [hp_X]/1 mL; ARANEUS DIADEMATUS 12 [hp_X]/1 mL; CARBO ANIMALIS 12 [hp_X]/1 mL; ACTIVATED CHARCOAL 12 [hp_X]/1 mL; ARTEMISIA CINA PRE-FLOWERING TOP 12 [hp_X]/1 mL; MERCURIUS SOLUBILIS 12 [hp_X]/1 mL; PODOPHYLLUM 12 [hp_X]/1 mL; SELENIUM 12 [hp_X]/1 mL; SPIGELIA ANTHELMIA WHOLE 12 [hp_X]/1 mL; VERATRUM ALBUM ROOT 12 [hp_X]/1 mL; BILIRUBIN 15 [hp_X]/1 mL; CREATINE 15 [hp_X]/1 mL; CREATININE 15 [hp_X]/1 mL; INDOLE 15 [hp_X]/1 mL; SKATOLE 15 [hp_X]/1 mL; PROTEUS MIRABILIS 20 [hp_X]/1 mL; SALMONELLA ENTERICA ENTERICA SEROVAR ENTERITIDIS 12 [hp_C]/1 mL
INACTIVE INGREDIENTS: WATER; ALCOHOL

DRUG FACTS:

ACTIVE INGREDIENTS:

Alfalfa 3X, Berberis Vulgaris 3X, Rhamnus Purshiana 3X, Rheum 3X, Taraxacum Officinale 3X, Hepar Bovine 8X, Small Intestine 8X, Aranea Diadema 12X, Carbo Animalis 12X, Carbo Vegetabilis 12X, CINA 12X, Mercurius Solubilis 12X, Podophyllum Peltatum 12X, Selenium Metallicum 12X, Spigelia Anthelmia 12X, Veratrum Album 12X, Bilirubin 15X, 30X, 200X, Creatine 15X, 30X, 200X, Creatinine 15X, 30X, 200X, Indolum 15X, 30X, 200X, Skatolum 15X, 30X, 200X, Proteus 20X, Morgan Gaertner 12C.

PURPOSE:

For temporary relief of flatulence associated with constipation.

WARNINGS:

If pregnant or breast-feeding, ask a health care professional before use.

Keep out of reach of children. In case of overdose, get medical help or contact a Poison Control Center right away.

Do not use if tamper evident seal is broken or missing. Store in cool, dry place.

KEEP OUT OF REACH OF CHILDREN:

In case of overdose, get medical help or contact a Poison Control Center right away.

DIRECTIONS:

10 drops orally, 3 times a day. Consult a physician for use in children under 12 years of age.

INDICATIONS:

For temporary relief of flatulence associated with constipation.

INACTIVE INGREDIENTS:

Demineralized Water, 25% Ethanol

QUESTIONS:

Distributed by:

BioActive Nutritional, Inc.

1803 N. Wickham Rd.

Melbourne, FL 32935

bioactivenutritional.com

PACKAGE LABEL DISPLAY:

BioActiveNutritional

COLOTOX

HOMEOPATHIC

1 FL OZ (30 ml)